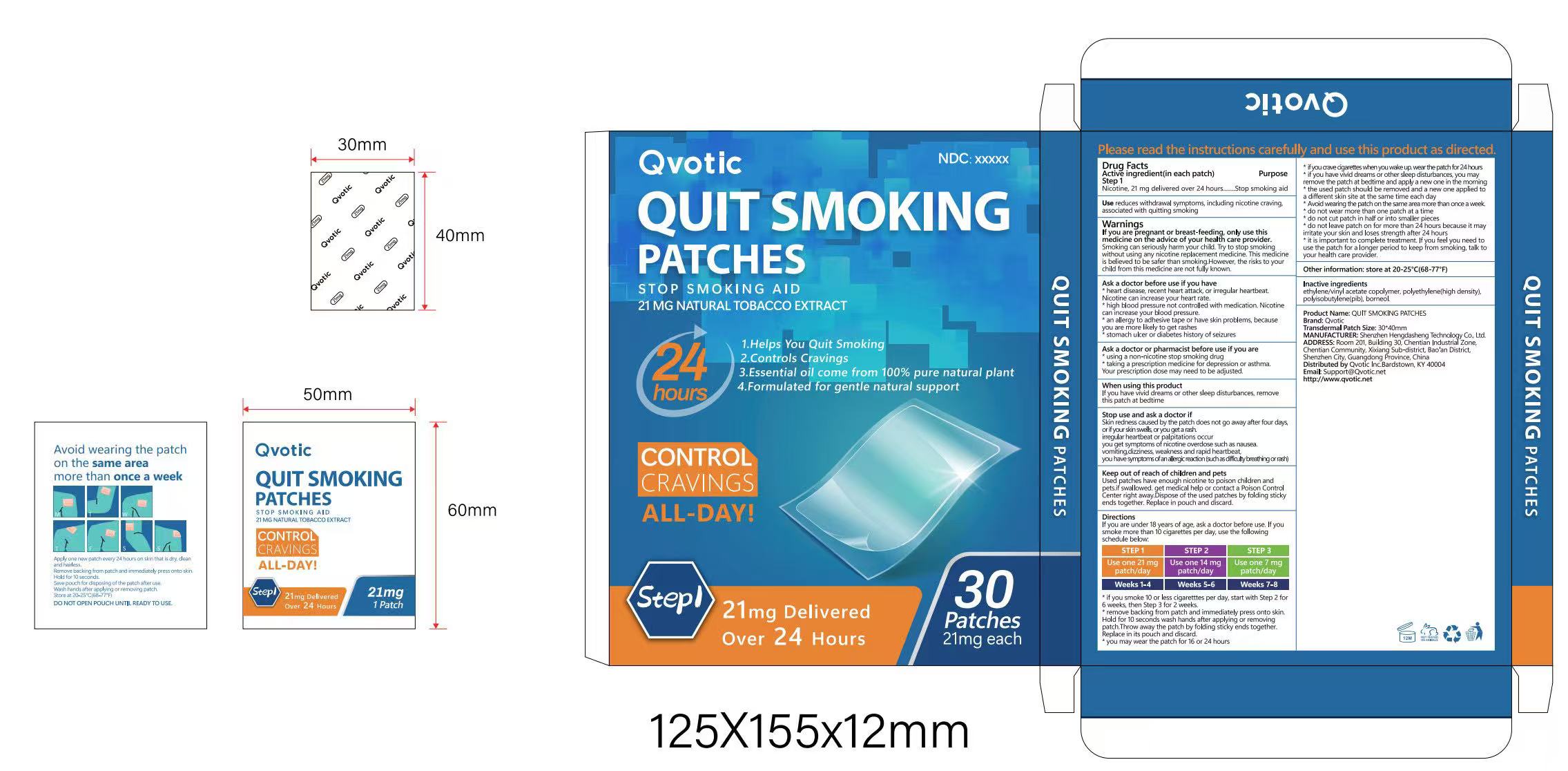 DRUG LABEL: QUIT SMOKING  21mg
NDC: 87308-006 | Form: PATCH
Manufacturer: Shenzhen Hengdasheng Technology Co., Ltd
Category: otc | Type: HUMAN OTC DRUG LABEL
Date: 20260122

ACTIVE INGREDIENTS: NICOTINE 2.4 mg/100 mg
INACTIVE INGREDIENTS: ETHYLENE-VINYL ACETATE COPOLYMER (15% VINYL ACETATE); HIGH DENSITY POLYETHYLENE; POLYISOBUTYLENE (1000 MW); BORNEOL

87308-006
21mg

Active Ingredient(s)

Nicotine, 21 mg delivered over 24 hours

Purpose

Stop smoking aid

Use

Use reduces withdrawal symptoms, including nicotine craving,associated with quitting smoking

Warnings

If you are pregnant or breast-feeding, only use thismedicine on the advice of your health care provider.

Smoking can seriously harm your child. Try to stop smokingwithout using any nicotine replacement medicine.

This medicine is believed to be safer than smoking.However, the risks to your child from this medicine are not fully known.

Do not use

* heart disease, recent heart attack, or irregular heartbeat.Nicotine can increase your heart rate.

* high blood pressure not controlled with medication. Nicotine can increase your blood pressure.

* an allergy to adhesive tape or have skin problems, because you are more likely to get rashes

* stomach ulcer or diabetes history of seizures

* using a non-nicotine stop smoking drug

* taking a prescription medicine for depression or asthma.

Your prescription dose may need to be adjusted.

WHEN USING

If you have vivid dreams or other sleep disturbances, remove this patch at bedtime

STOP USE

Skin redness caused by the patch does not go away after four days,

or ifyour skin swells, oryou get a rash.irregular heartbeat or palpitations

occuryou get symptoms of nicotine overdose such as nausea.vomiting,

dizziness, weakness and rapid heartbeat,you have symptoms of an allergic

reaction (such as difficulty breathing or rash)

KEEP OUT OF REACH OF CHILDREN

Used patches have enough nicotine to poison children and pets.if swallowed.

get medical help or contact a Poison Control Center right away.Dispose of the

used patches by folding sticky ends together. Replace in pouch and discard.

Directions

If you are under 18 years of age, ask a doctor before use. If you smoke more than 10

cigarettes per day, use the following schedule below:

STEP1:Use one 21 mg patch/day---Weeks 1-4

STEP2:Use one 14 mg patch/day---Weeks 5-6

STEP3:Use one 7 mg patch/day---Weeks 7-8

* if you smoke 10 or less cigaretttes per day, start with Step2 for6 weeks, then Step 3 for 2 weeks.

* remove backing from patch and immediately press onto skin.Hold for 10 seconds wash hands

after applying or removingpatch.Throw away the patch by folding sticky ends together.Replace in its pouch and discard.

* you may wear the patch for 16 or 24 hours

* ifyou crave cigarettes when you wake up. wear the patch for 24 hours

* if you have vivid dreams or other sleep disturbances, you mayremove the patch at bedtime

and apply a new one in the morning

* the used patch should be removed and a new one applied to a different skin site at the same time each day

*Avoid wearing the patch on the same area more than once a week.*do not wear more than one patch at a time

* do not cut patch in half or into smaller pieces

* do not leave patch on for more than 24 hours because it may irritate your skin and loses strength after 24 hours

* it is important to complete treatment. If you feel you need to use the patch for a longer period to keep from smoking,

talk to your health care provider.

Other information

store at 20-25°C(68-77°F)

Inactive ingredients

ethylene/vinyl acetate copolymer, polyethylene(high density),polyisobutylene(pib), borneol.